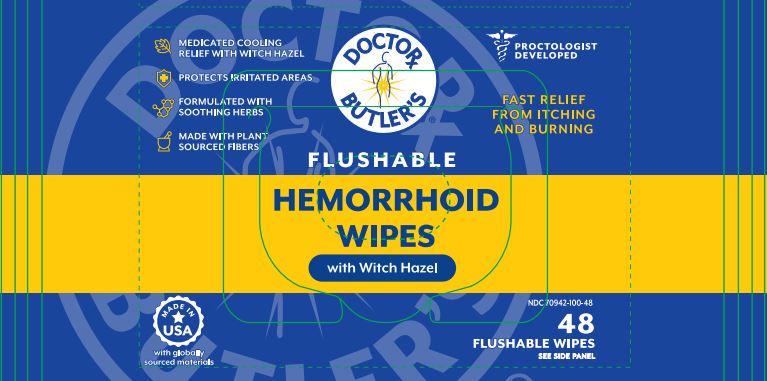 DRUG LABEL: Dr Butlers Hemorrhoid
NDC: 70942-100 | Form: SWAB
Manufacturer: Beyond Health, PA
Category: otc | Type: HUMAN OTC DRUG LABEL
Date: 20250723

ACTIVE INGREDIENTS: WITCH HAZEL 50 g/100 g
INACTIVE INGREDIENTS: ROSEMARY; CHAMOMILE; LYSINE; WATER; GLYCERYL CAPRYLATE; SODIUM CITRATE; BETAINE; CALENDULA OFFICINALIS FLOWER; CAPRYLHYDROXAMIC ACID; GLYCERIN

Doctor Butler's Hemorrhoid Wipes

Active Ingredieni

Organic Witch Hazel 50%

Purpose

Astringent

Uses

- Helps relieve the local itching and discomfort associated with hemorrhoids
- Temporay relief of irritation and burning
- Aids in protecting irritated anorectal areas

Warnings

For external use only.

When using this product

- do not exceed the recommended daily dosage unless directed by a doctor
- do not put this product into the rectum using fingers or any mechanical device or applicator

Stop use and ask a doctor if

- bleeding occurs
- condition worsens or does not improve within 7 days

Keep out of reach of children.

If swallowed, get medical help or contact a Poison Control Center right away. (1-800-222-1222)

Directions

- adults: unfold wipe and cleanse the area by gently wiping, patting or blotting. If necessary, repeat until all matter is removed from the area.
- use up to 6 times daily or after each bowel movement and before applying additional hemorrhoidal treatments, and then discard.
- children under 12 years of age: consult a doctor
- flush or dispose of wipe in trash
- for best results, flush no more than one wipe at a time.

Othet Information

- store at room temperature 20-25ºC (68-77ºF)
- for use as moist compress - first cleanse the area as previously described. Fold wipe to desired size and place in contact with skin tissue. Leave in place for 15 minutes and repeat as needed.

Inactive Ingredients

Purified Water

Tocopherol

Rosmarinus Officinalis (Rosemary) Leaf Extract

Lysine

Calendula Officinalis Flower Extract

Chamomilla Recutita (Matricaria) Flower Extract

Sodium Citrate

Betaine

Caprylhydroxamic Acid

Glyceryl Caprylate

Glycerin